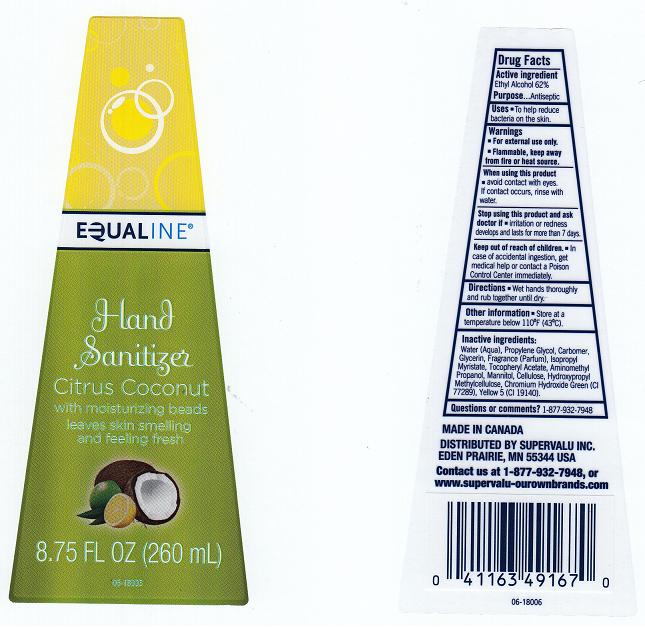 DRUG LABEL: EQUALINE
NDC: 41163-258 | Form: LIQUID
Manufacturer: SUPERVALU INC.
Category: otc | Type: HUMAN OTC DRUG LABEL
Date: 20120629

ACTIVE INGREDIENTS: ALCOHOL 62 mL/100 mL
INACTIVE INGREDIENTS: WATER; PROPYLENE GLYCOL; CARBOMER 934; GLYCERIN; ISOPROPYL MYRISTATE; ALPHA-TOCOPHEROL ACETATE; AMINOMETHYLPROPANOL; MANNITOL; POWDERED CELLULOSE; HYPROMELLOSE 2208 (4000 MPA.S); CHROMIC OXIDE; FD&C YELLOW NO. 5

DRUG FACTS

ACTIVE INGREDIENT

ETHYL ALCOHOL 62%

PURPOSE

ANTISEPTIC

USES

TO HELP REDUCE BACTERIA ON THE SKIN.

WARNINGS

FOR EXTERNAL USE ONLY. FLAMMABLE. KEEP AWAY FROM FIRE OR HEAT SOURCE.

WHEN USING THIS PRODUCT

AVOID CONTACT WITH EYES. IF CONTACT OCCURS, RINSE WITH WATER.

STOP USING THIS PRODUCT AND ASK DOCTOR IF

IRRITATION OR REDNESS DEVELOPS AND LASTS FOR MORE THAN 7 DAYS.

KEEP OUT OF REACH OF CHILDREN

IN CASE OF ACCIDENTAL INGESTION, GET MEDICAL HELP OR CONTACT A POISON CONTROL CENTER IMMEDIATELY.

DIRECTIONS

WET HANDS THOROUGHLY AND RUB TOGETHER UNTIL DRY.

OTHER INFORMATION

STORE AT A TEMPERATURE BELOW 110F (43C).

INACTIVE INGREDIENTS:

WATER (AQUA), PROPYLENE GLYCOL, CARBOMER, GLYCERIN, FRAGRANCE (PARFUM), ISOPROPYL MYRISTATE, TOCOPHERYL ACETATE, AMINOMETHYL PROPANOL, MANNITOL, CELLULOSE, HYDROXYPROPYL METHYLCELLULOSE, CHROMIUM HYDROXIDE GREEN (CI 77289), YELLOW 5 (CI 19140).

Questions or comments?

1-877-932-7948